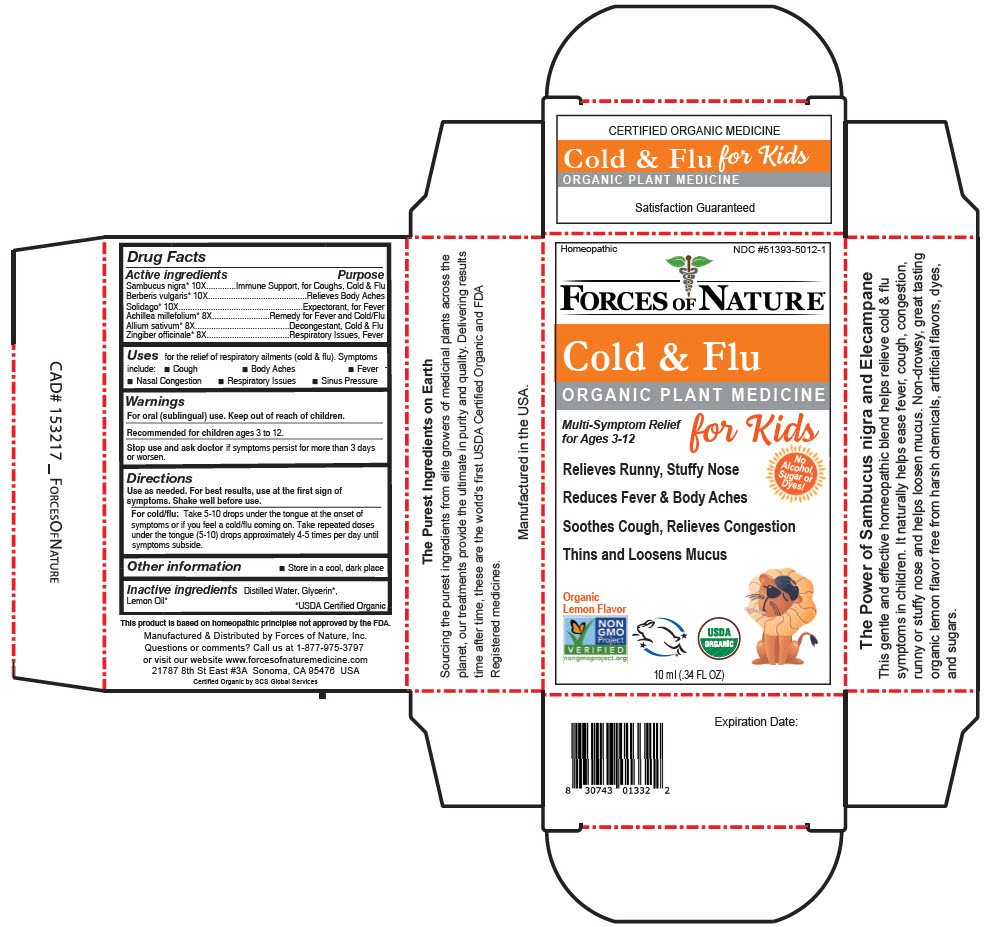 DRUG LABEL: Cold and Flu Kids
NDC: 51393-5012 | Form: SOLUTION/ DROPS
Manufacturer: Forces of Nature
Category: homeopathic | Type: HUMAN OTC DRUG LABEL
Date: 20221205

ACTIVE INGREDIENTS: EUROPEAN ELDERBERRY 10 [hp_X]/100 mL; BERBERIS VULGARIS ROOT 10 [hp_X]/100 mL; SOLIDAGO CANADENSIS FLOWERING TOP 10 [hp_X]/100 mL; ACHILLEA MILLEFOLIUM FLOWERING TOP 8 [hp_X]/100 mL; GARLIC 8 [hp_X]/100 mL; GINGER 8 [hp_X]/100 mL
INACTIVE INGREDIENTS: WATER; Glycerin; LEMON OIL, COLD PRESSED

Cold & Flu Kids

Drug Facts

ACTIVE INGREDIENT

Active ingredients | Purpose
Sambucus nigra [USDA Certified Organic] 10X | Immune Support, for Coughs, Cold & Flu
Berberis vulgaris 10X | Relieves Body Aches
Solidago 10X | Expectorant, for Fever
Achillea millefolium 8X | Remedy for Fever and Cold/Flu
Allium sativum 8X | Decongestant, Cold & Flu
Zingiber officinale 8X | Respiratory Issues, Fever

Uses

for the relief of respiratory ailments (cold & flu). Symptoms include:

- Cough
- Body Aches
- Fever
- Nasal Congestion
- Respiratory Issues
- Sinus Pressure

Warnings

KEEP OUT OF REACH OF CHILDREN

For oral (sublingual) use. Keep out of reach of children.

Recommended for children ages 3 to 12.

Stop use and ask doctor if symptoms persist for more than 3 days or worsen.

Directions

Use as needed. For best results, use at the first sign of symptoms. Shake well before use.

For cold/flu

Take 5-10 drops under the tongue at the onset of symptoms or if you feel a cold/flu coming on. Take repeated doses under the tongue (5-10) drops approximately 4-5 times per day until symptoms subside.

Other information

- Store in a cool, dark place

Inactive ingredients

Distilled Water, Glycerin, Lemon Oil

Questions or comments?

Call us at 1-877-975-3797 or visit our website www.forcesofnaturemedicine.com

Manufactured & Distributed by Forces of Nature, Inc.
21787 8th St East #3A Sonoma, CA 95476 USA

PRINCIPAL DISPLAY PANEL - 10 ml Bottle Carton

Homeopathic
NDC #51393-5012-1

FORCES OF NATURE®

Cold & Flu

ORGANIC PLANT MEDICINE

Multi-Symptom Relief
for Ages 3-12

for Kids

Relieves Runny, Stuffy Nose

Reduces Fever & Body Aches

Soothes Cough, Relieves Congestion

Thins and Loosens Mucus

No
Alcohol,
Sugar or
Dyes!

Organic
Lemon Flavor

NON
GMO
Project
VERIFIED
nongmoproject.org

USDA
ORGANIC

10 ml (.34 FL OZ)